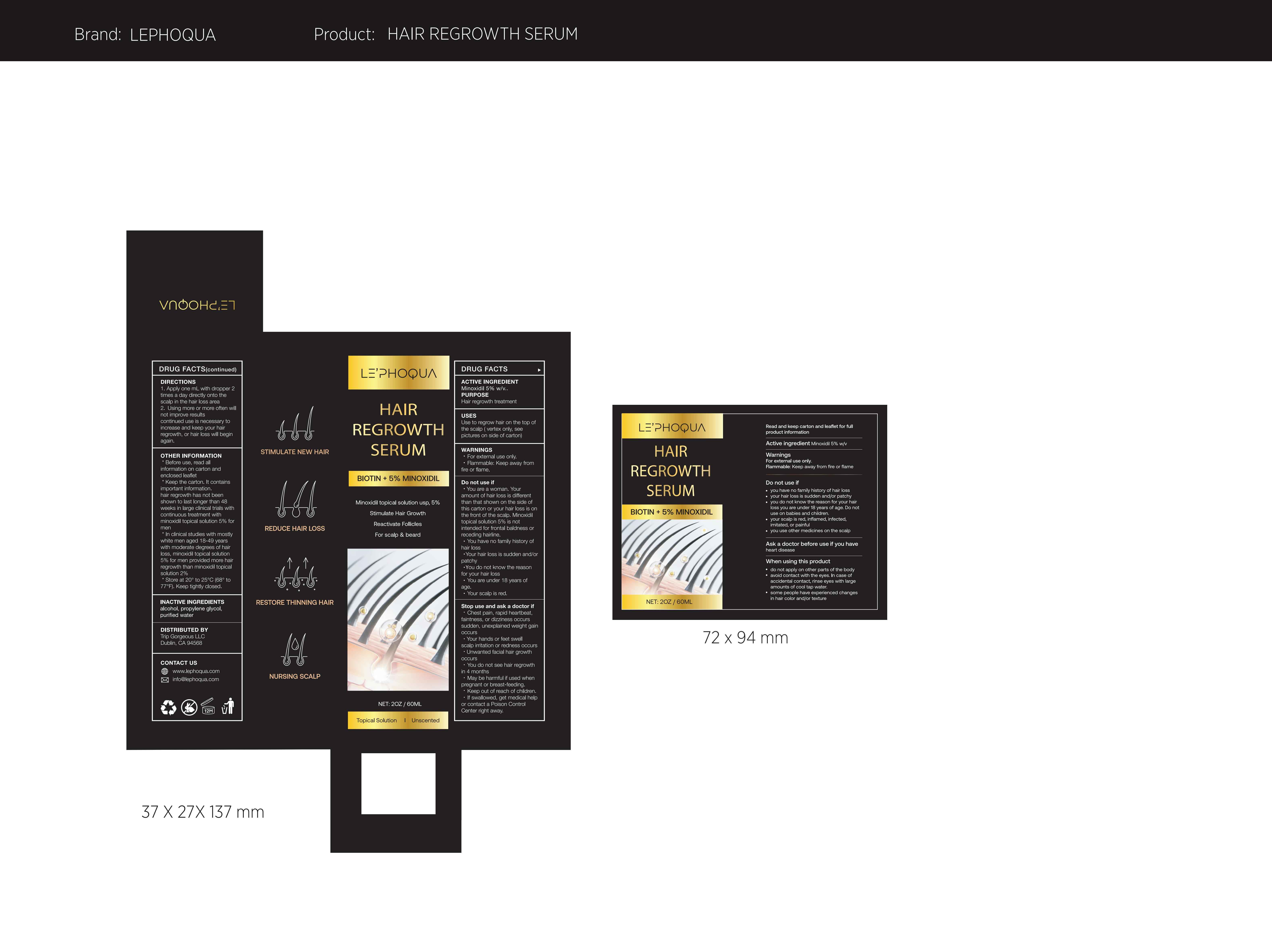 DRUG LABEL: LE PHOQUA Hair Regrowth Serum BIOTIN 5% MINOXIDIL
NDC: 83565-007 | Form: LIQUID
Manufacturer: Stellans Inc.
Category: otc | Type: HUMAN OTC DRUG LABEL
Date: 20231125

ACTIVE INGREDIENTS: MINOXIDIL 5 g/100 mL
INACTIVE INGREDIENTS: PROPYLENE GLYCOL; ALCOHOL; WATER

Active Ingredient

Minoxidil 5% w/v............Hair Regrowth Treatment

Purpose

Hair Regrowth Treatment

Use

Use to regrow hair on the top of the scalp (vertex only, see pictures on side of carton)

Warnings

·For external use only.
·Flammable: Keep away from fire or flame.

Do not use

·You are a woman. Your amount of hair loss is different than that shown on the side of this carton or your hair loss is on the front of the scalp. Minoxidil topical solution 5% is not intended for frontal baldness or receding hairline.
·You have no family history of hair loss
·Your hair loss is sudden and/or patchy
·You do not know the reason for your hair loss
·You are under 18 years of age.
·Your scalp is red.

Stop Use

·Chest pain, rapid heartbeat, faintness , or dizziness occurs
sudden, unexplained weight gain occurs
·Your hands or feet swell scalp irritation or redness occurs
·Unwanted fa cial hair growth occurs
·You do not see hair regrowth in 4 months
·May be harmful if used when pregnant or breast-feeding.
·Keep out of reach of children,
·If swallowed, get medical help or contact a Poison Control Center right away.

Keep Oot Of Reach Of Children

Do not place this product within the reach of children

Directions

1. Apply 1 ml with dropper2 times a day directly onto the scalp in the hair loss area.

2. Using more or more often will not improve results continued use is necessary to increase and keep your hair regrowth, or hair loss will begin again.
check grammar

Other information

*Before use, read all information on carton and
enclosed leaflet
*Keep the carton. It contains important information.
hair regrowth has not been shown to last longer than 48 weeks in large clinical trials with continuous treatment with minoxidill topical solution 5% for men
*In clinical studies with mostly white men aged 18-49 years with moderate degrees of hair loss, minoxidil topical solution 5% for men provided more hair regrowth than minoxidil topical solution 2%
*Store at 20°to 25℃(68°to 77°F). Keep tightly closed.

Inactive ingredients

Alcohol

Propylene Glycol

Purified Water

Questions

CONTACT US
www.lephoqua.com
info@lephoqua.com